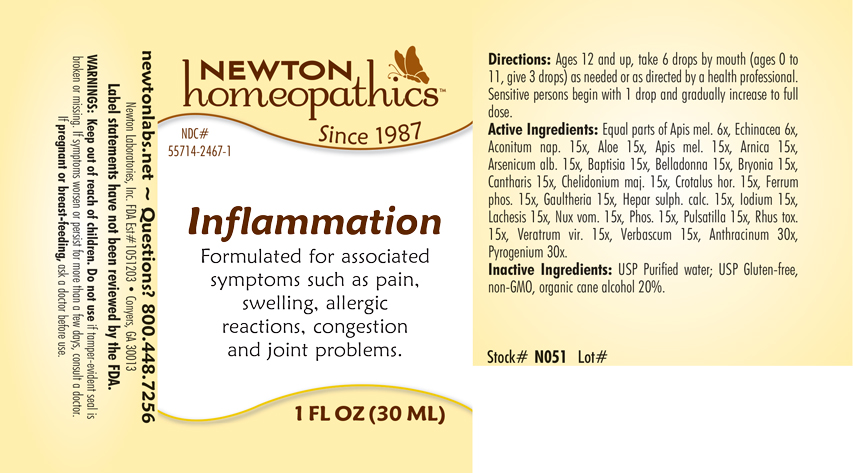 DRUG LABEL: Inflammation
NDC: 55714-2467 | Form: LIQUID
Manufacturer: Newton Laboratories, Inc.
Category: homeopathic | Type: HUMAN OTC DRUG LABEL
Date: 20250827

ACTIVE INGREDIENTS: ALOE 15 [hp_X]/1 mL; BACILLUS ANTHRACIS IMMUNOSERUM RABBIT 30 [hp_X]/1 mL; RANCID BEEF 30 [hp_X]/1 mL; ACONITUM NAPELLUS 15 [hp_X]/1 mL; APIS MELLIFERA 15 [hp_X]/1 mL; ARNICA MONTANA 15 [hp_X]/1 mL; ARSENIC TRIOXIDE 15 [hp_X]/1 mL; BAPTISIA TINCTORIA ROOT 15 [hp_X]/1 mL; ATROPA BELLADONNA 15 [hp_X]/1 mL; BRYONIA ALBA ROOT 15 [hp_X]/1 mL; LYTTA VESICATORIA 15 [hp_X]/1 mL; CHELIDONIUM MAJUS 15 [hp_X]/1 mL; CROTALUS HORRIDUS HORRIDUS VENOM 15 [hp_X]/1 mL; FERROSOFERRIC PHOSPHATE 15 [hp_X]/1 mL; GAULTHERIA PROCUMBENS TOP 15 [hp_X]/1 mL; CALCIUM SULFIDE 15 [hp_X]/1 mL; IODINE 15 [hp_X]/1 mL; LACHESIS MUTA VENOM 15 [hp_X]/1 mL; STRYCHNOS NUX-VOMICA SEED 15 [hp_X]/1 mL; PHOSPHORUS 15 [hp_X]/1 mL; ANEMONE PULSATILLA 15 [hp_X]/1 mL; TOXICODENDRON PUBESCENS LEAF 15 [hp_X]/1 mL; VERATRUM VIRIDE ROOT 15 [hp_X]/1 mL; VERBASCUM THAPSUS 15 [hp_X]/1 mL; ECHINACEA, UNSPECIFIED 6 [hp_X]/1 mL
INACTIVE INGREDIENTS: WATER; ALCOHOL

Inflammation 2467L

INDICATIONS & USAGE SECTION

Formulated for symptoms such as pain, swelling, allergic reactions, congestion and joint problems.

DOSAGE & ADMINISTRATION SECTION

Directions: Ages 12 and up, take 6 drops by mouth (ages 0 to 11, give 3 drops) as needed or as directed by a health professional. Sensitive persons begin with 1 drop and gradually increase to full dose.

OTC - ACTIVE INGREDIENT SECTION

Equal parts of Apis mellifica 6x, Echinacea 6x, Aconitum napellus 15x, Aloe 15x, Apis mellifica 15x, Arnica montana 15x, Arsenicum album 15x, Baptisia tinctoria 15x, Belladonna 15x, Bryonia 15x, Cantharis 15x, Chelidonium majus 15x, Crotalus horridus 15x, Ferrum phosphoricum 15x, Gaultheria procumbens 15x, Hepar sulphuris calcareum 15x, Iodium 15x, Lachesis mutus 15x, Nux vomica 15x, Phosphorus 15x, Pulsatilla 15x, Rhus toxicodendron 15x, Veratrum viride 15x, Verbascum thapsus 15x, Anthracinum 30x, Pyrogenium 30x.

OTC - PURPOSE SECTION

Formulated for symptoms such as pain, swelling, allergic reactions, congestion and joint problems..

INACTIVE INGREDIENT SECTION

Inactive Ingredients: USP Purified Water; USP Gluten-free, non-GMO, organic cane alcohol 20%.

QUESTIONS SECTION

newtonlabs.net – Questions? 800.448.7256

Newton Laboratories, Inc. FDA Est # 1051203 - Conyers, GA 30013

WARNINGS SECTION

WARNINGS: Keep out of reach of children. Do not use if tamper-evident seal is broken or missing. If symptoms worsen or persist for more than a few days, consult a doctor. If pregnant or breast-feeding, ask a doctor before use.

OTC - PREGNANCY OR BREAST FEEDING SECTION

If pregnant or breast-feeding, ask a doctor before use.

OTC - KEEP OUT OF REACH OF CHILDREN SECTION

Keep out of reach of children